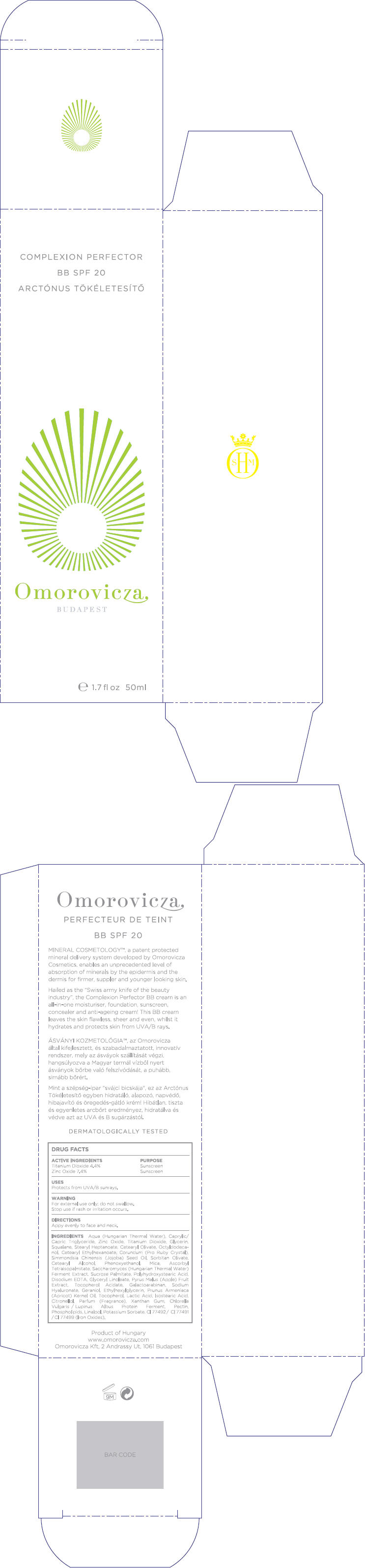 DRUG LABEL: Complexion Perfector BB SPF20
NDC: 41442-143 | Form: CREAM
Manufacturer: Omorovicza Kozmetikai Kft.
Category: otc | Type: HUMAN OTC DRUG LABEL
Date: 20120216

ACTIVE INGREDIENTS: Titanium Dioxide 2.2 mL/50 mL; Zinc Oxide 3.7 mL/50 mL
INACTIVE INGREDIENTS: Water; Caprylic/Capric Mono/Diglycerides; Glycerin; Squalane; Stearyl Heptanoate; Cetearyl Olivate; Octyldodecanol; Cetearyl Ethylhexanoate; Aluminum Oxide; Sorbitan Olivate; Cetostearyl Alcohol; Phenoxyethanol; Mica; Sucrose Palmitate; Edetate Disodium; Glyceryl Monolinoleate; Apple; Hyaluronate Sodium; Geraniol; Ethylhexylglycerin; Apricot Kernel Oil; Tocopherol; Lactic Acid; Glyceryl Isostearate; .Beta.-Citronellol, (+/-)-; Xanthan Gum; Pectin; Linalool, (+)-; Potassium Sorbate; Ferrosoferric Oxide

Complexion Perfector BB SPF20

DRUG FACTS

ACTIVE INGREDIENT

ACTIVE INGREDIENTS | PURPOSE
Titanium Dioxide 4.4% | Sunscreen
Zinc Oxide 7.4% | Sunscreen

USES

Protects from UVA/B sunrays.

WARNING

For external use only; do not swallow.

Stop use if rash or irritation occurs.

DIRECTIONS

Appy evenly to face and neck.

INGREDIENTS

Aqua (Hungarian Thermal Water), Caprylic/Capric Triglyceride, Zinc Oxide, Titanium Dioxide, Glycerin, Squalane, Stearyl Heptanoate, Cetearyl Olivate, Octyldodecanol, Cetearyl Ethylhexanoate, Corundum (Pro Ruby Crystal), Simmondsia Chinensis (Jojoba) Seed Oil, Sorbitan Olivate, Cetearyl Alcohol, Phenoxyethanol, Mica, Ascorbyl Tetraisopalmitate, Saccharomyces (Hungarian Thermal Water) Ferment Extract, Sucrose Palmitate, Polyhydroxystearic Acid, Disodium EDTA, Glyceryl Linoleate, Pyrus Malus (Apple) Fruit Extract, Tocopherol Acidate, Galactoarabinan, Sodium Hyaluronate, Geraniol, Ethylhexylglycerin, Prunus Armeniaca (Apricot) Kernel Oil, Tocopherol, Lactic Acid, Isostearic Acid, Citronellol, Parfum (Fragrance), Xanthan Gum, Chlorella Vulgaris / Lupinus Albus Protein Ferment, Pectin, Phospholipids, Linalool, Potassium Sorbate, CI 77492/ CI 77491/ CI 77499 (Iron Oxides).

PRINCIPAL DISPLAY PANEL - 50 ml Carton

COMPLEXION PERFECTOR

BB SPF 20

Omorovicza
BUDAPEST

e 1.7 fl oz 50ml